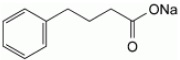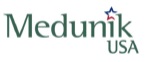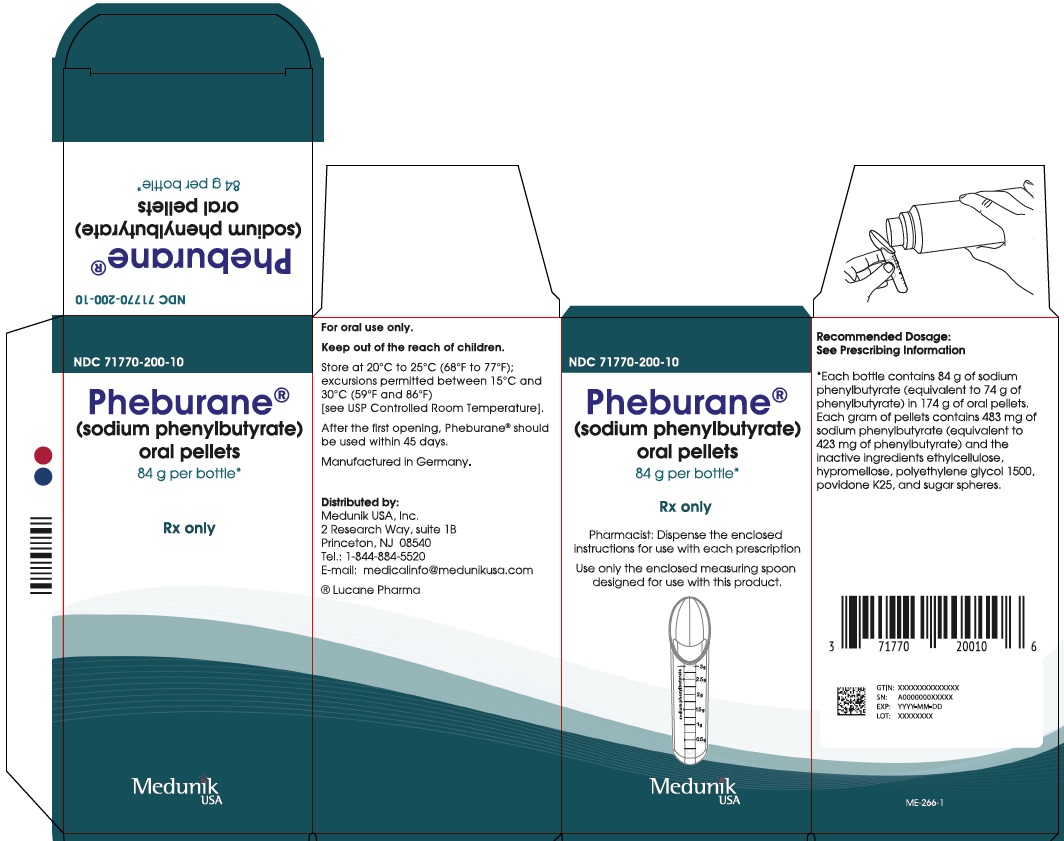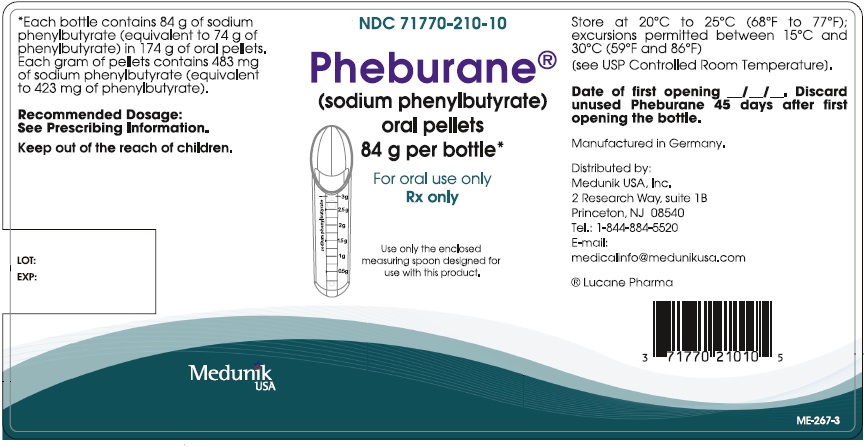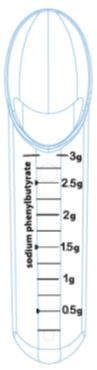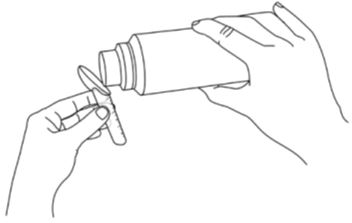 DRUG LABEL: PHEBURANE
NDC: 71770-210 | Form: PELLET
Manufacturer: Medunik USA
Category: prescription | Type: HUMAN PRESCRIPTION DRUG LABEL
Date: 20251126

ACTIVE INGREDIENTS: SODIUM PHENYLBUTYRATE 483 mg/1 g
INACTIVE INGREDIENTS: ETHYLCELLULOSES; HYPROMELLOSE 2910 (3 MPA.S); POLYETHYLENE GLYCOL 1500; STARCH, CORN; POVIDONE K25; SUCROSE

HIGHLIGHTS OF PRESCRIBING INFORMATION

These highlights do not include all the information needed to use PHEBURANE safely and effectively. See full prescribing information for PHEBURANE.
PHEBURANE® (sodium phenylbutyrate) oral pellets
Initial U.S. Approval: 1996

1 INDICATIONS AND USAGE

PHEBURANE is a nitrogen-binding agent indicated as adjunctive therapy to standard of care, which includes dietary management, for the chronic management of adult and pediatric patients with urea cycle disorders (UCDs), involving deficiencies of carbamylphosphate synthetase (CPS), ornithine transcarbamylase (OTC) or argininosuccinic acid synthetase (AS). (1)

Limitations of Use
PHEBURANE is not indicated for the treatment of acute hyperammonemia. (1)

2 DOSAGE AND ADMINISTRATION

- PHEBURANE treatment should be supervised by a healthcare provider experienced in the treatment of UCDs. For administration, see full prescribing information. (2.1, 2.4)
- The recommended dosage measured as sodium phenylbutyrate is:
  - Patients weighing < 20 kg: 450–600 mg/kg/day of sodium phenylbutyrate orally. (2.1)
  - Patients weighing ≥ 20 kg: 9.9–13.0 g/m^2/day of sodium phenylbutyrate orally. (2.1)
- Monitor plasma ammonia levels to determine the need for dosage adjustment. (2.2)
- Monitor patients for potential neurotoxicity. (2.2)
- For patients with hepatic impairment, start at the lower end of the recommended dosing range. (2.3)

3 DOSAGE FORMS AND STRENGTHS

Oral pellets: 84 g of sodium phenylbutyrate per bottle. (3)

4 CONTRAINDICATIONS

None. (4)

5 WARNINGS AND PRECAUTIONS

- Neurotoxicity of Phenylacetate: Increased exposure to phenylacetate, the major metabolite of PHEBURANE, may be associated with neurotoxicity in patients with UCDs. Consider reducing the dose if neurotoxicity symptoms are present. (5.1)
- Hypokalemia: Renal excretion of phenylacetylglutamine may induce urinary loss of potassium. Monitor serum potassium during therapy and initiate appropriate treatment when necessary. (5.2)
- Conditions Associated with Edema: Calculate the total amount of sodium patients will be exposed to based on their weight or body surface area. If a patient develops new-onset edema or worsening edema while on treatment, discontinue administration of PHEBURANE and initiate appropriate therapy. (5.3)
- Diabetes Mellitus, Hereditary Fructose Intolerance, Glucose-Galactose Malabsorption or Sucrase-Isomaltase Insufficiency: Avoid use of PHEBURANE in patients with rare hereditary problems of fructose intolerance, glucose-galactose malabsorption or sucrase-isomaltase insufficiency. (5.4)

6 ADVERSE REACTIONS

Most common adverse reactions (incidence ≥ 3%) are menstrual dysfunction, decreased appetite, body odor and bad taste or taste aversion. (6)

To report SUSPECTED ADVERSE REACTIONS, contact Medunik USA, Inc. at 1-844-884-5520 or FDA at 1-800-FDA-1088 or www.fda.gov/medwatch.

7 DRUG INTERACTIONS

- Valproic Acid, Haloperidol, or Corticosteroids: May increase plasma ammonia level; monitor ammonia levels closely. (7.1)
- Probenecid: May inhibit renal excretion of metabolites of PHEBURANE including phenylacetate and phenylacetylglutamine; monitor for potential neurotoxicity. (7.2)

FULL PRESCRIBING INFORMATION

1 INDICATIONS AND USAGE

PHEBURANE is indicated as adjunctive therapy to standard of care, which includes dietary management, for the chronic management of adult and pediatric patients with urea cycle disorders (UCDs), involving deficiencies of carbamylphosphate synthetase (CPS), ornithine transcarbamylase (OTC) or argininosuccinic acid synthetase (AS).

Limitations of Use

Episodes of acute hyperammonemia may occur in patients while on PHEBURANE. PHEBURANE is not indicated for the treatment of acute hyperammonemia, which can be a life-threatening medical emergency that requires rapid acting interventions to reduce plasma ammonia levels.

2 DOSAGE AND ADMINISTRATION

2.1 Recommended Dosage

PHEBURANE treatment should be supervised by a healthcare provider experienced in the treatment of urea cycle disorders.

The recommended dosage of PHEBURANE (measured as sodium phenylbutyrate) for patients with urea cycle disorders is:

- Patients weighing less than 20kg: 450 – 600 mg/kg/day of sodium phenylbutyrate orally. Divide the calculated total daily dose into three to six doses. Administer as three to six divided doses and take with food.
- Patients weighing greater than or equal to 20 kg: 9.9 – 13 g/m^2/day of sodium phenylbutyrate orally. Divide the calculated total daily dose into three to six doses. Administer as three to six divided doses and take with food.

The maximum dosage is 20 grams per day. Combine PHEBURANE with dietary protein restriction and, in some cases, amino acid supplementation (e.g., essential amino acids, arginine, citrulline, and protein-free calorie supplements).

Measure the dose using only the calibrated spoon provided in the packaging. This calibrated dosing spoon directly measures PHEBURANE oral pellets as sodium phenylbutyrate [see Dosage and Administration (2.4)].

If a dose is missed, take the missed dose as soon as possible. There should be at least 3 hours between two doses and doses should not be doubled to make up for the missed dose.

2.2 Dosage Adjustment and Monitoring

Monitor plasma ammonia levels to determine the need for dosage adjustment. Adjust the PHEBURANE dosage to maintain the plasma ammonia level within the normal range for the patient’s age, taking into consideration their clinical condition (e.g., nutritional requirements, protein intake, growth parameters, etc.).

Monitor patients for potential neurotoxicity and obtain measurements of plasma phenylacetate and phenylacetylglutamine levels [see Warnings and Precautions (5.1), Adverse Reactions (6)]. If neurologic symptoms (e.g. vomiting, nausea, headache, somnolence or confusion) are present in the absence of high ammonia levels or other intercurrent illnesses, consider reducing the dose of PHEBURANE.

2.3 Dosage Adjustment in Patients with Hepatic Impairment

For patients with hepatic impairment, start at the lower end of the recommended dosing range and maintain patients on the lowest dose necessary to control plasma ammonia levels [see Use in Specific Populations (8.7)].

2.4 Administration Instructions

For oral administration only. Administration via gastrostomy or nasogastric tubes has not been evaluated.

1. Schedule PHEBURANE dosages at the same time as food consumption (meal or snack).
2. Use the calibrated dosing spoon to measure PHEBURANE oral pellets. The dosing spoon is directly calibrated in grams of sodium phenylbutyrate.
3. Swallow the coated oral pellets with a drink (e.g., water, fruit juices, protein-free infant formulas) or sprinkle onto spoonful of apple sauce or carrot puree. Do not chew PHEBURANE oral pellets directly or mix into liquids.
4. Swallow immediately to minimize dissolution of coating.

Administration of PHEBURANE oral pellets with other foods has not been studied and is not recommended. Additionally, administration with soft food is only recommended in patients old enough to consume soft foods.

3 DOSAGE FORMS AND STRENGTHS

Oral pellets: 84 g of sodium phenylbutyrate per PHEBURANE bottle as white to off-white coated pellets.

4 CONTRAINDICATIONS

None

5 WARNINGS AND PRECAUTIONS

5.1 Neurotoxicity of Phenylacetate

Increased exposure to phenylacetate, the major metabolite of PHEBURANE, may be associated with neurotoxicity in patients with UCDs. In a study of adult cancer patients receiving intravenous phenylacetate, 250-300 mg/kg/day for 14 days, repeated at 4-week intervals, signs and symptoms of neurotoxicity, which were reversible upon discontinuation, were seen at plasma concentrations ≥ 3.5 mmol/L, and included somnolence, fatigue, and light headedness [see Adverse Reactions (6)]. PHEBURANE is not approved for intravenous use or for treatment of patients with cancer.

If symptoms of vomiting, nausea, headache, somnolence or confusion are present in the absence of high ammonia levels or other intercurrent illnesses, consider reducing the dose of PHEBURANE [see Dosage and Administration (2.2)].

Phenylacetate caused neurotoxicity when given subcutaneously in rat pups [see Use in Specific Populations (8.4)].

5.2 Hypokalemia

Renal excretion of phenylacetylglutamine may induce urinary loss of potassium. Monitor serum potassium during therapy and initiate appropriate treatment when necessary.

5.3 Conditions Associated with Edema

PHEBURANE contains 124 mg (5.4 mmol) of sodium per gram of sodium phenylbutyrate, corresponding to 2.5 g (108 mmol) of sodium in the maximum daily dose of 20 g of sodium phenylbutyrate. In order to decide if administration of PHEBURANE is appropriate in patients with diseases that involve edema such as heart failure, cirrhosis, or nephrosis, calculate the total amount of sodium patients will be exposed to based on their weight or body surface area (BSA) [see Dosage and Administration (2.1)]. If a patient develops new-onset edema or worsening edema while on treatment, discontinue administration of PHEBURANE and initiate appropriate therapy.

5.4 Diabetes Mellitus, Hereditary Fructose Intolerance, Glucose-Galactose Malabsorption or Sucrase-Isomaltase Insufficiency

PHEBURANE contains 768 mg of sucrose per gram of sodium phenylbutyrate, corresponding to 15.4 g of sucrose in the maximum daily dose of 20 g of sodium phenylbutyrate. This should be considered in patients with diabetes mellitus. Avoid use of PHEBURANE in patients with rare hereditary problems of fructose intolerance, glucose-galactose malabsorption or sucrase-isomaltase insufficiency.

6 ADVERSE REACTIONS

The following adverse reactions associated with the use of sodium phenylbutyrate were identified in clinical studies or postmarketing reports. Because some of these reactions were reported voluntarily and from a population of uncertain size, it is not always possible to reliably estimate their frequency or establish a causal relationship to drug exposure.

Most common adverse reactions (incidence ≥ 3%) are amenorrhea or menstrual dysfunction (irregular menstrual cycles), decreased appetite, body odor and bad taste or taste aversion.

Less Common Clinical Adverse Reactions

Blood and lymphatic system disorders: aplastic anemia, ecchymoses

Cardiac disorders: arrhythmia

Gastrointestinal disorders: abdominal pain, decreased appetite, gastritis, nausea and vomiting, constipation, rectal bleeding, peptic ulcer disease, pancreatitis

Metabolism and nutrition disorders: increased weight, edema

Nervous system disorders: syncope, headache

Psychiatric disorders: depression

Renal and urinary disorders: renal tubular acidosis

Skin and subcutaneous tissue disorders: rash

Laboratory Adverse Reactions

Blood and lymphatic system disorders: anemia, leukopenia and leukocytosis, thrombocytopenia, thrombocytosis

Hepatobiliary disorders: hyperbilirubinemia, increased blood alkaline phosphatase, increased transaminases

Metabolism and nutrition disorders: acidosis, alkalosis, hyperchloraemia, hypophosphataemia, hyperuricemia, hyperphosphatemia, hypernatremia, hypokalemia, hypoalbuminemia, decreased total protein

Clinical Adverse Reactions with Use of Phenylacetate

Nervous system disorders: Neurotoxicity was reported in cancer patients receiving intravenous phenylacetate, the major metabolite of PHEBURANE (PHEBURANE is not approved for intravenous use or for treatment of patients with cancer). Signs and symptoms were predominately somnolence, fatigue, and dizziness (lightheadedness); less frequently reported were headache, dysgeusia, hypoacusis, disorientation, memory impairment, and exacerbation of a pre-existing neuropathy.

7 DRUG INTERACTIONS

7.1 Potential for Other Drugs to Affect Ammonia

Corticosteroids

Use of corticosteroids may cause the breakdown of body protein and increase plasma ammonia levels.

Valproic Acid and Haloperidol

Hyperammonemia may be induced by haloperidol and by valproic acid.

Monitor plasma ammonia levels closely when corticosteroids, valproic acid, or haloperidol is used concomitantly with PHEBURANE.

7.2 Potential for Other Drugs to Affect PHEBURANE

Probenecid

Probenecid may inhibit renal excretion of the metabolites of PHEBURANE including phenylacetate and phenylacetylglutamine. Monitor patients for potential neurotoxicity and measure plasma phenylacetate and phenylacetylglutamine levels when probenecid is used concomitantly with PHEBURANE [see Dosage and Administration (2.2)].

8 USE IN SPECIFIC POPULATIONS

8.1 Pregnancy

Risk Summary

Available data with sodium phenylbutyrate use in pregnant women are insufficient to identify a drug associated risk of major birth defects, miscarriage or adverse maternal or fetal outcomes. Animal reproduction studies have not been conducted with sodium phenylbutyrate. Based on published animal data, phenylacetate may be neurotoxic to the developing brain (see Data).

There are serious risks to the mother and fetus associated with untreated urea cycle disorders during pregnancy which can result in serious morbidity and mortality to the mother and fetus (see Clinical Considerations).

The estimated background risk of major birth defects and miscarriage for the indicated population is unknown. All pregnancies have a background risk of birth defect, loss or other adverse outcomes. In the U.S. general population, the estimated background risk of major birth defects and miscarriage in clinically recognized pregnancies is 2% to 4% and 15% to 20%, respectively.

Clinical Considerations

Disease-Associated Maternal and/or Embryo/Fetal Risk

Pregnancy is a time of increased metabolic demand which increases the risk for hyperammonemic episodes when metabolic demands are not met. Hyperammonemic episodes in pregnancy are associated with impaired cognition in the mother and an increased risk of maternal and fetal death.

Data

In rats, intrauterine exposure to phenylacetate produced lesions in the neonatal brain in layer 5 of the cortical pyramidal cells; dendritic spines were longer and thinner than normal and reduced in number.

8.2 Lactation

Risk Summary

There are no data on the presence of sodium phenylbutyrate and its metabolite in either human or animal milk, the effects on the breastfed infant, or the effects on milk production. The developmental and health benefits of breastfeeding should be considered along with the mother’s clinical need for PHEBURANE and any potential adverse effects on the breastfed infant from PHEBURANE or from the underlying maternal condition.

8.4 Pediatric Use

The safety and effectiveness of PHEBURANE have been established as adjunctive therapy to the standard of care, which includes dietary management, in the chronic management of pediatric patients with urea cycle disorders (UCDs), involving deficiencies of carbamylphosphate synthetase (CPS), ornithine transcarbamylase (OTC) or argininosuccinic acid synthetase (AS).

PHEBURANE is not indicated for the treatment of acute hyperammonemia, which can be a life-threatening medical emergency that requires rapid acting interventions to reduce plasma ammonia levels.

The sodium content of PHEBURANE has the potential to cause new-onset edema or worsening edema from salt and water retention, particularly in patients with underlying predisposing conditions [see Warnings and Precautions (5.3)].

Neurotoxicity has been observed in juvenile animals with phenylacetate exposure [see Warnings and Precautions (5.1)].

Juvenile Animal Toxicity Data

When given subcutaneously to rat pups, 190–474 mg/kg phenylacetate caused decreased proliferation and increased loss of neurons, and it reduced CNS myelin. Cerebral synapse maturation was retarded, and the number of functioning nerve terminals in the cerebrum was reduced, which resulted in impaired brain growth.

8.5 Geriatric Use

Clinical studies of PHEBURANE did not include sufficient numbers of subjects aged 65 and over to determine whether they respond differently from younger subjects. Other reported clinical experience has not identified differences in responses between the elderly and younger patients. In general, dose selection for an elderly patient should be cautious, usually starting at the low end of the dosing range, reflecting the greater frequency of decreased hepatic, renal, or cardiac function and of concomitant disease or other drug therapy.

8.6 Renal Impairment

No studies with PHEBURANE were conducted in subjects with renal impairment. Monitor plasma ammonia levels when starting patients with impaired renal function on PHEBURANE [see Clinical Pharmacology (12)].

8.7 Hepatic Impairment

No studies with PHEBURANE were conducted in subjects with hepatic impairment. Start at the lower end of the recommended dosing range and maintain patients with hepatic impairment on the lowest dose necessary to control plasma ammonia levels [see Clinical Pharmacology (12.3), Dosage and Administration (2.3)].

10 OVERDOSAGE

Overdoses of PHEBURANE exceeding ten-fold the maximum recommended dosage may produce emesis, CNS depression, metabolic acidosis with or without respiratory alkalosis, hypernatremia, hypokalemia, and hypophosphatemia. Symptoms of overdose overlap with those of acute hyperammonemia. If overdose occurs, discontinue PHEBURANE, monitor plasma phenylacetate and ammonia levels closely, and institute appropriate emergency management, which may include hemodialysis, continuous veno-venous hemofiltration (CVVH) or extracorporeal membrane oxygenation (ECMO).

11 DESCRIPTION

PHEBURANE (sodium phenylbutyrate) oral pellets is a nitrogen binding agent. Sodium phenylbutyrate is a white or yellowish-white powder, freely soluble in water and in methanol, and practically insoluble in methylene chloride. It is known chemically as sodium 4-phenylbutanoate with a molecular weight of 186.19 and the molecular formula C10H11NaO2.

Structural formula:

Each bottle of PHEBURANE contains 84 g of sodium phenylbutyrate (equivalent to 74 g of phenylbutyrate) in 174 g of oral pellets. Each gram of pellets contains 483 mg of sodium phenylbutyrate (equivalent to 423 mg of phenylbutyrate). PHEBURANE contains the following inactive ingredients: ethylcellulose, hypromellose, polyethylene glycol 1500, povidone K25, and sugar spheres.

12 CLINICAL PHARMACOLOGY

12.1 Mechanism of Action

Sodium phenylbutyrate is a pro-drug and is metabolized to phenylacetate. Phenylacetate is a metabolically-active compound that conjugates with glutamine via acetylation to form phenylacetylglutamine. Phenylacetylglutamine is excreted by the kidneys, hence providing an alternate vehicle for waste nitrogen excretion.

12.2 Pharmacodynamics

In patients with urea cycle disorders, sodium phenylbutyrate decreased elevated plasma ammonia and glutamine levels.

12.3 Pharmacokinetics

The pharmacokinetics of phenylbutyrate and its metabolite phenylacetate were characterized in healthy adult subjects following a single oral administration of PHEBURANE (3 g of sodium phenylbutyrate) under fasted and fed conditions.

Absorption

Under fasted condition, the mean (SD) maximum plasma concentration (Cmax) of phenylbutyrate ranged from 146 (30) to 169 (33) μg/mL, which was achieved at approximately 0.6 hour after PHEBURANE administration. The mean (SD) area under the plasma concentration-time curve (AUC) of phenylbutyrate ranged from 272 (78) to 283 (68) h*μg/mL.

Effect of Food

Compared to fasted condition, AUC of phenylbutyrate decreased by 40-45% and Cmax of phenylbutyrate decreased by 55%, when PHEBURANE was administered with a high-fat, high-calorie meal (total 800 to 1000 calories with approximately 150, 250, and 500-600 calories from protein, carbohydrate, and fat, respectively). When PHEBURANE was administered with a normal-fat, normal-calorie, low-protein meal (total 600 to 700 calories with approximately 60, 200, and 400 calories from protein, fat, and carbohydrate, respectively), AUC of phenylbutyrate decreased by 56-63% and Cmax decreased by 43-45% compared to fasted condition.

Elimination

The mean half-life of phenylbutyrate ranged from 0.5 to 0.8 hour.

Metabolism

Following oral administration, sodium phenylbutyrate is metabolized by β-oxidation into phenylacetate, which is converted to its coenzyme A ester, phenylacetyl-coenzyme A and further conjugated with glutamine to form phenylacetylglutamine. Phenylacetylglutamine is excreted by the kidneys. The major sites for metabolism of sodium phenylbutyrate are the liver and kidneys. Phenylacetate is also hydrolysed by esterases in liver and blood.

Excretion

Approximately 80–100% of sodium phenylbutyrate is excreted by the kidneys within 24 hours as phenylacetylglutamine. For each gram of sodium phenylbutyrate administered, it is estimated that between 0.12–0.15 grams of phenylacetylglutamine nitrogen are produced.

Specific Populations

Patients with Renal Impairment or Hepatic Impairment

PHEBURANE has not been studied in patients with renal impairment or in patients with hepatic impairment.

Drug Interaction Studies

In vitro or clinical studies with PHEBURANE for determination of potential drug-drug interaction have not been conducted.

13 NONCLINICAL TOXICOLOGY

13.1 Carcinogenesis, Mutagenesis, Impairment of Fertility

Carcinogenicity, mutagenicity, and fertility studies of sodium phenylbutyrate have not been conducted.

16 HOW SUPPLIED/STORAGE AND HANDLING

PHEBURANE (sodium phenylbutyrate) oral pellets consists of white to off-white pellets and is available in a child-resistant high-density polyethylene (HDPE) bottle with a desiccant in the cap.

Each bottle contains 84 g of sodium phenylbutyrate (equivalent to 74 g of phenylbutyrate) in 174 g of oral pellets (NDC 71770-200-10). Each gram of pellets contains 483 mg of sodium phenylbutyrate (equivalent to 423 mg of phenylbutyrate).

A calibrated measuring spoon that dispenses up to 3 g of sodium phenylbutyrate in increments of 0.25 g is provided in the packaging.

Store PHEBURANE at 20°C to 25°C (68°F to 77°F); excursions permitted between 15°C and 30°C (59°F and 86°F) [see USP Controlled Room Temperature].

Discard any remaining PHEBURANE 45 days after first opening of the bottle.

17 PATIENT COUNSELING INFORMATION

Advise the patient to read the FDA-approved patient labeling (Patient Information and Instructions for Use).

Neurotoxicity

Advise the patient or caregiver that neurotoxicity may occur during PHEBURANE treatment. Inform the patient or caregiver of the signs and symptoms of this risk and to contact the healthcare provider immediately if signs and symptoms occur [see Warnings and Precautions (5.1)].

Administration

Instruct the patient or caregiver to only use the calibrated dosing spoon supplied with PHEBURANE to measure the oral pellets. Inform the patient or caregiver that the dosing spoon is directly calibrated in grams of sodium phenylbutyrate. Inform the patient or caregiver to consume the pellets immediately after preparation [see Dosage and Administration (2.4)].

Inform the patient or caregiver that if a dose is missed, take the missed dose as soon as possible. Instruct the patient or caregiver that there should be at least 3 hours between two doses and doses should not be doubled to make up for the missed dose [see Dosage and Administration (2.1)].

Storage and Handling

Advise the patient or caregiver to discard any remaining PHEBURANE 45 days after first opening of the bottle.

Distributed by:
Medunik USA, Inc.
2 Research Way, Suite 1B
Princeton, NJ 08540

PHEBURANE® is a registered trademark of Lucane Pharma

Patient Information

PHEBURANE (FE bue rayne)

(sodium phenylbutyrate)

oral pellets

What is PHEBURANE?

- PHEBURANE is a prescription medicine, used along with a specific diet, for the long-term management of adults and children with urea cycle disorders (UCDs), involving deficiencies of carbamylphosphate synthetase (CPS), ornithine transcarbamylase (OTC) or argininosuccinate synthetase (AS).
- Episodes of sudden, rapid increase of ammonia in the blood (acute hyperammonemia) may happen in people during treatment with PHEBURANE. PHEBURANE is not used for the treatment of acute hyperammonemia, which can be life-threatening and requires emergency medical treatment.

Before taking PHEBURANE, tell your or your child’s healthcare provider about all of your medical conditions, including if you:

- have heart problems.
- have kidney or liver problems.
- have diabetes (PHEBURANE contains sucrose), or have a history of fructose intolerance, glucose-galactose malabsorption, or sucrase-isomaltase insufficiency.
- are pregnant or plan to become pregnant. It is not known if PHEBURANE will harm your unborn baby.
- are breastfeeding or plan to breastfeed. It is not known if PHEBURANE passes into your breastmilk. Talk to your healthcare provider about the best way to feed your baby during treatment with PHEBURANE.

Tell your healthcare provider about all the medicines you or your child take, including prescription and over-the-counter medicines, vitamins, and herbal supplements.

Certain medicines may increase the level of ammonia in your blood or cause serious side effects when taken during treatment with PHEBURANE. Especially tell your healthcare provider if you or your child take:

- corticosteroids
- valproic acid
- haloperidol
- probenecid

Know the medicines you take. Keep a list of them to show your or your child’s healthcare provider and pharmacist when you get a new medicine.

How should I take PHEBURANE?

Read the detailed Instructions for Use that comes with PHEBURANE for information about the right way to prepare and take a dose of PHEBURANE.

- Take PHEBURANE exactly as prescribed by your healthcare provider.
- Your healthcare provider may change your dose if needed. Do not change your dose unless your healthcare provider tells you to.
- Your healthcare provider will prescribe PHEBURANE based on your or your child’s weight.
- Schedule your PHEBURANE dose at the same time you eat a meal or snack.
- Use the calibrated dosing spoon to measure PHEBURANE oral pellets.
- PHEBURANE oral pellets should be taken with a drink such as water, fruit juices or protein-free infant formulas, orsoft food, such as apple sauce or carrot puree. It is not recommended to use other foods to take your dose of PHEBURANE oral pellets.
- Do not chew PHEBURANE oral pellets directly or mix PHEBURANE oral pellets into liquids.
- If you miss a dose of PHEBURANE, take it as soon as possible. Each dose of PHEBURANE should be taken at least 3 hours apart. If you have missed a dose within 3 hours of the next dose, take only one dose the next time it is scheduled.
- Do not give or take PHEBURANE through a gastrotomy or nasogastric tube.
- If you take too much PHEBURANE, call your healthcare provider or Poison Help line at 1-800-222-1222, or go to the nearest hospital emergency room right away.

What are the possible side effects of PHEBURANE?

PHEBURANE can cause serious side effects, including:

Nervous system problems (neurotoxicity). Call your healthcare provider right away if get any of the following symptoms during treatment with PHEBURANE:

- sleepiness
- tiredness
- lightheadedness
- vomiting

- nausea
- headache
- confusion

Low potassium levels in your blood (hypokalemia). Your healthcare provider will monitor your blood potassium levels during treatment with PHEBURANE and treat if needed.

Conditions related to swelling (edema). PHEBURANE contains salt (sodium), which can cause swelling from salt and water retention. Your healthcare provider will decide if PHEBURANE is right for you if you have certain medical conditions that can cause swelling, such as heart failure, liver problems or kidney problems.

The most common side effects of PHEBURANE include:

- absent or irregular menstrual periods
- decreased appetite

- body odor
- bad taste or avoiding foods that you ate prior to getting sick (taste aversion)

Your healthcare provider may do certain blood tests to check you or your child for side effects during treatment with PHEBURANE.

These are not all of the possible side effects of PHEBURANE.

Call your doctor for medical advice about side effects. You may report side effects to FDA at 1-800-FDA-1088.

How should I store PHEBURANE?

- Store PHEBURANE at room temperature between 68°F and 77°F (20°C and 25°C).
- PHEBURANE comes in a child-resistant bottle. The bottle cap contains a desiccant to help keep PHEBURANE dry.
- Throw away (discard) any remaining PHEBURANE 45 days after first opening of the bottle.

Keep PHEBURANE and all medicines out of the reach of children.

General information about the safe and effective use of PHEBURANE.

Medicines are sometimes prescribed for purposes other than those listed in a Patient Information leaflet. Do not use PHEBURANE for a condition for which it was not prescribed. Do not give PHEBURANE to other people, even if they have the same symptoms that you have. It may harm them. You can ask your healthcare provider or pharmacist for information about PHEBURANE that is written for health professionals.

What are the ingredients in PHEBURANE?

Active ingredient: sodium phenylbutyrate

Inactive Ingredients: ethylcellulose, hypromellose, polyethylene glycol 1500, povidone K25, and sugar spheres.

Distributed by: Medunik USA, Inc., 2 Research Way, Suite 1B, Princeton, NJ 08540

For more information, go to www.medunikusa.com

This Patient Information has been approved by the U.S. Food and Drug Administration. | Issued: August 2023

INSTRUCTIONS FOR USE
PHEBURANE®(FE bue rayne)
(sodium phenylbutyrate)
oral pellets

Read this Instructions for Use before taking PHEBURANE oral pellets and each time you get a refill. There may be new information. This Instructions for Use does not take the place of talking to your healthcare provider about your medical condition or treatment. Talk to your healthcare provider or pharmacist if you have any questions about how to take a dose of PHEBURANE.

This Instructions for Use contains information on how to measure and take PHEBURANE.

Figure A: Calibrated dosing spoon provided
with PHEBURANE

Important information you need to know before taking PHEBURANE

- The total daily dose of PHEBURANE must be given in divided doses and taken with food (meal or snack). Your healthcare provider will tell you when to take PHEBURANE and the dose to take.
- Schedule PHEBURANE doses at the same time as eating a meal or snack.
- Only use the calibrated dosing spoon provided with PHEBURANE to measure the dose (See Figure A).

Supplies needed for measuring and taking PHEBURANE

- Bottle of PHEBURANE oral pellets.
- Calibrated dosing spoon provided with PHEBURANE.
- A drink such as water, fruit juices or protein-free infant formulas, orsoft food, such as apple sauce or carrot puree. It is not recommended to use other foods to take your dose of PHEBURANE oral pellets.

Measuring PHEBURANE

Repeat Steps 1 through 3 throughout the day as prescribed by your healthcare provider to get the total daily dose.

Step 1

- Use the calibrated dosing spoon to measure the prescribed divided dose of PHEBURANE oral pellets (See Figure A).

The calibrated dosing spoon measures PHEBURANE oral pellets as grams (g) of sodium phenylbutyrate. The calibrated dosing spoon dispenses up to 3 g of sodium phenylbutyrate, in increments of 0.25 g.

- Pour the oral pellets directly into the calibrated dosing spoon until it reaches the black line for the prescribed dose of sodium phenylbutyrate in grams (See Figure B).

Figure B: Pour the PHEBURANE oral
pellets directly into the calibrated
dosing spoon.

Taking PHEBURANE

Step 2

- Tap the bottom of the calibrated dosing spoon 1 time on a hard surface to give a flat level of oral pellets and continue filling until you reach the prescribed dose.

Step 3

- Swallow PHEBURANE oral pellets with a drink such as water, fruit juices, or protein-free infant formulas.

or

- Sprinkle PHEBURANE oral pellets onto a spoonful of apple sauce or carrot puree and swallow right away. It is important to swallow right away to prevent coating from dissolving.

Do not chew PHEBURANE oral pellets directly or mix PHEBURANE oral pellets into liquids.

If the prescribed divided dose is more than 3 grams, repeat Steps 1 through 3 to get the prescribed divided dose of sodium phenylbutyrate.

Storing PHEBURANE

- Store PHEBURANE at room temperature between 68°F and 77°F (20°C and 25°C).
- PHEBURANE comes in a child-resistant bottle. The bottle cap contains a desiccant to help keep PHEBURANE dry.
- Throw away (discard) any remaining PHEBURANE 45 days after first opening of the bottle.
- Keep PHEBURANE and all medicines out of the reach of children.

Disposing of PHEBURANE

- Throw away (dispose of) the bottle of PHEBURANE 45 days after first opening by dropping off the medicine at a drug take back site or following the steps below.
  - Mix medicine with an unappealing substance such as dirt, cat litter, or used coffee grounds
  - Place the mixture in a container such as a sealed plastic bag
  - Throw away the container in your trash at home, and
  - Delete all personal information on the prescription label of the empty medicine bottle, then throw away or recycle the empty bottle.
- Throw away (dispose of) used calibrated dosing spoon in the household trash.
- Do not use the calibrated dosing spoon to measure any other medicine.

If cleaning is necessary, rinse the calibrated dosing spoon with water and dry it completely.

To replace the calibrated dosing spoon, contact Medunik USA at 1-844-884-5520.

Distributed by: Medunik USA, Inc. 2 Research Way, Suite 1B, Princeton, NJ 08540

PHEBURANE® is a registered trademark of Lucane Pharma.

This Instructions for Use has been approved by the U.S. Food and Drug Administration. | Issued: August 2023

PRINCIPAL DISPLAY PANEL - Carton

NDC 71770-200-10

Pheburane®

(sodium phenylbutyrate)
oral pellets

84 g per bottle*

Rx only

Pharmacist: Dispense the enclosed
instructions per use with each prescription

Use only the enclosed measuring spoon
designed for use with this product.

Medunik USA

PRINCIPAL DISPLAY PANEL - Container

NDC 71770-210-10

Pheburane®

(sodium phenylbutyrate)
oral pellets

84 g per bottle*

For oral use only
Rx only

Use only the enclosed
measuring spoon designed for
use with this product.